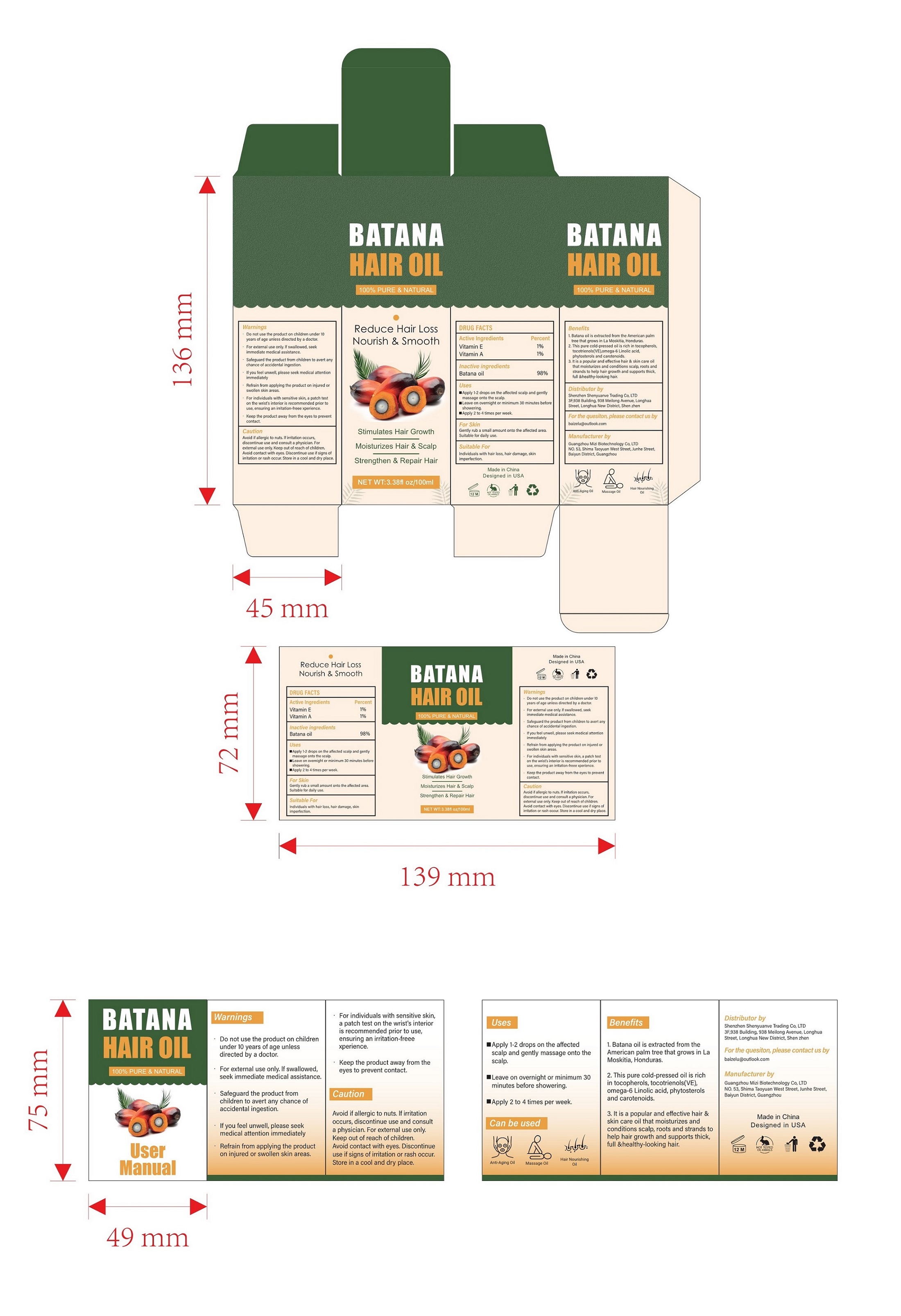 DRUG LABEL: Batana hair oil
NDC: 84336-003 | Form: OIL
Manufacturer: Shenzhen Shenyuanye Trading Co., LTD
Category: otc | Type: HUMAN OTC DRUG LABEL
Date: 20240624

ACTIVE INGREDIENTS: .ALPHA.-TOCOPHEROL 1 mg/100 mL; VITAMIN A 1 mg/100 mL
INACTIVE INGREDIENTS: PALM OIL

Batana hair oil

ACTIVE INGREDIENT

Vitamin E------1%
Vitamin A------1%

PURPOSE

moisturizes and conditions scalp, roots andstrands to help hair growth and supports thick,full &healthy-looking hair.

INDICATIONS AND USAGE

Suitable For Individuals with hair loss, hair damage, skinimperfection.

For Skin Gently rub a small amount onto the affected area. Suitable for daily use.

Warnings

Do not use the product on children under 10 years of age unless directed by a doctor.

For external use only. If swallowed, seek immediate medical assistance.

Safeguard the product from children to avert any chance of accidental ingestion.

lf you feel unwell, please seek medical attention immediately.

For externaluse only.

DO NOT USE

Refrain from applying the product on injured or swollen skin areas.

WHEN USING

For individuals with sensitive skin, a patch teston the wrist's interior is recommended prior touse, ensuring an irritation-freee xperience.

STOP USE

Avoid if allergic to nuts, lf irritation occurs,discontinue use and consult a physician.

Avoid contact with eyes. Discontinue use if signs ofirritation or rash occur.

Keep out of reach of children

DOSAGE AND ADMINISTRATION

Apply 1-2 drops on the affected scalp and gently massage onto the scalp.
Leave on overnight or minimum 30 minutes before showering.
Apply 2 to 4 times per week.

INACTIVE INGREDIENT

Batana oil

QUESTIONS

Email at: baizelu@outlook.com